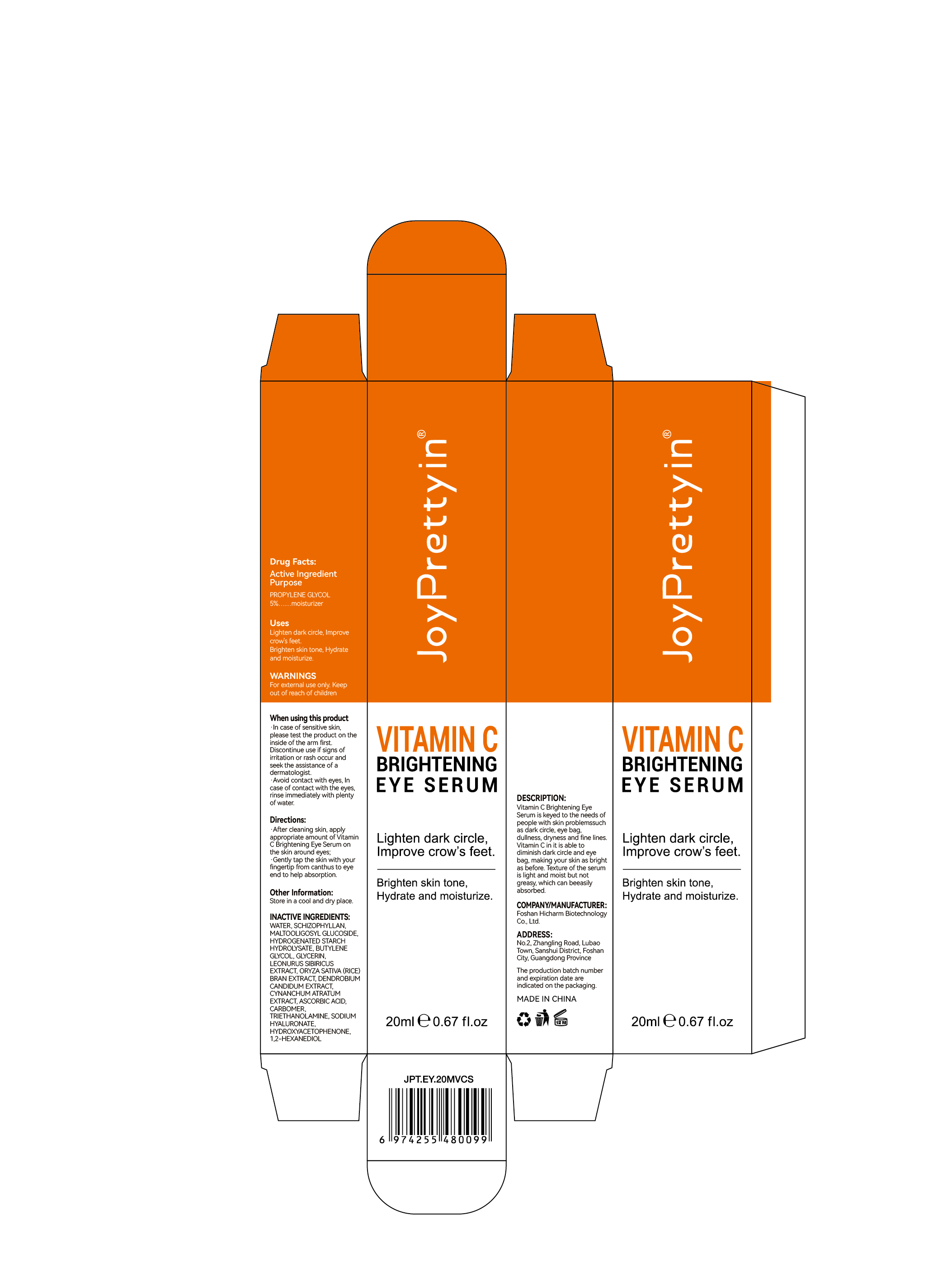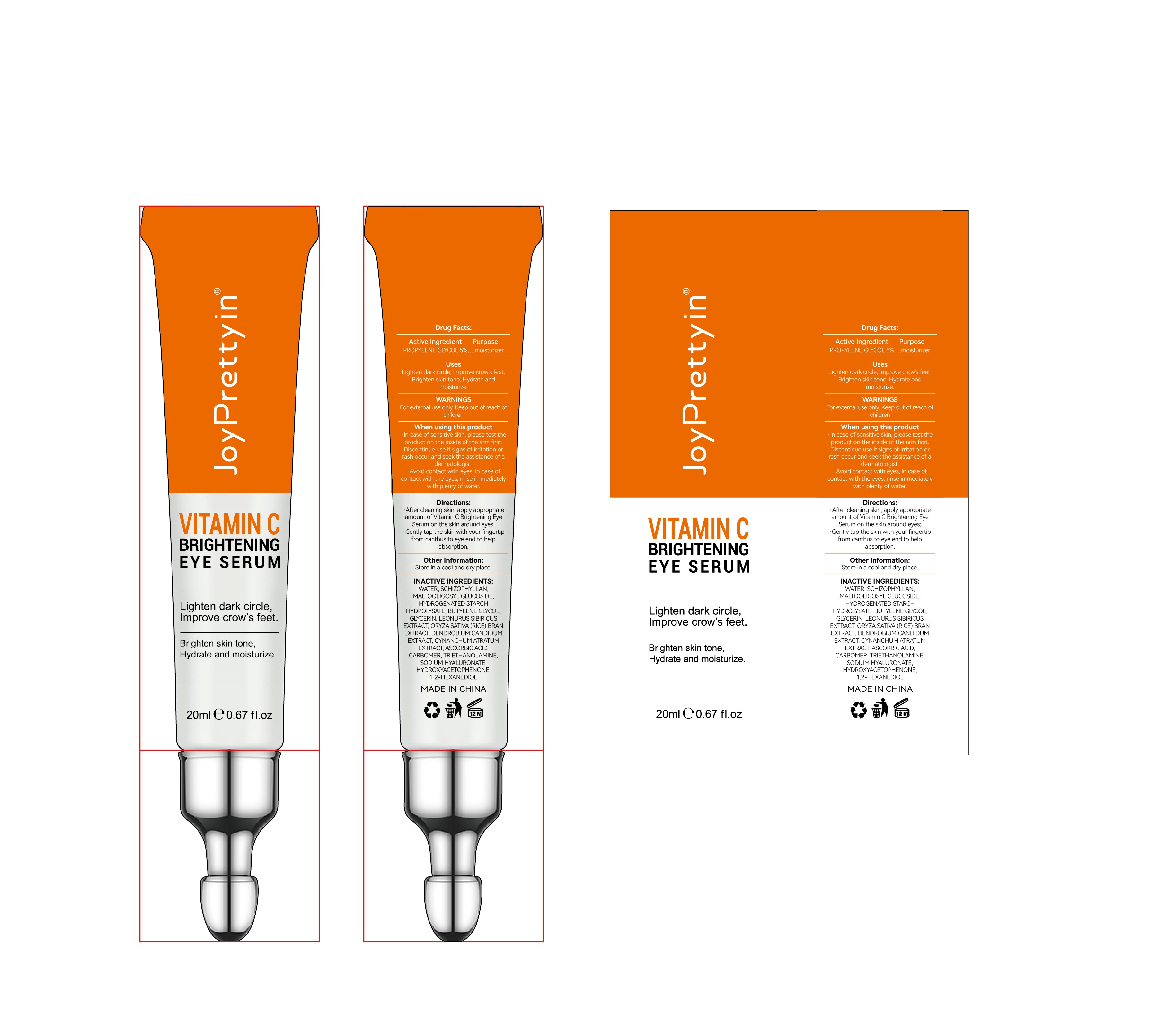 DRUG LABEL: JoyPrettyin VITAMIN C BRIGHTENING EYE SERUM
NDC: 84186-002 | Form: CREAM
Manufacturer: Guangzhou Bonnieco Cosmetics Co., Ltd
Category: otc | Type: HUMAN OTC DRUG LABEL
Date: 20240319

ACTIVE INGREDIENTS: PROPYLENE GLYCOL 5 g/100 mL
INACTIVE INGREDIENTS: WATER; HYDROGENATED STARCH HYDROLYSATE; CARBOMER HOMOPOLYMER, UNSPECIFIED TYPE; TROLAMINE; GLYCERIN; DENDROBIUM MONILIFORME WHOLE; SIZOFIRAN; MALTOOLIGOSYL GLUCOSIDE; LEONURUS SIBIRICUS LEAF; RICE BRAN; VINCETOXICUM ATRATUM STEM; HYALURONATE SODIUM; BUTYLENE GLYCOL; HYDROXYACETOPHENONE; 1,2-HEXANEDIOL; ASCORBIC ACID

84186-002

Active Ingredient

PROPYLENE GLYCOL 5%

Purpose

Lighten dark circle,Improve crow's feet.
Brighten skin tone, Hydrate and moisturize.

Use

Apply gently to skin and spread evenly

Warnings

·In case of sensitive skin, please test the product on the inside of the arm first. Discontinue use if signs of irritation or rash occur and seek the assistance of a dermatologist.
·Avoid contact with eyes, In case of contact with the eyes, rinse immediately with plenty of water.

Do not use

In case of sensitive skin, please test the product on the inside of the arm first.

When Using

In case of contact with the eyes, rinse immediately with plenty of water.

Keep Oot Of Reach Of Children

If swallowed, get medical help or contact a poison control center right away.

Directions

·After cleaning skin, apply appropriate amount of Vitamin C Brightening Eye Serum on the skin around eyes;
·Gently tap the skin with your fingertip from canthus to eye end to help absorption.

Other information

DESCRIPTION:
Vitamin C Brightening Eye Serum is keyed to the needs of people with skin problemssuch as dark circle, eye bag, dullness, dryness and fine lines. Vitamin C in it is able to diminish dark circle and eye bag, making your skin as bright as before. Texture of the serum is light and moist but not greasy, which can beeasily absorbed.

Inactive ingredients

WATER, SCHIZOPHYLLAN, MALTOOLIGOSYL GLUCOSIDE, HYDROGENATED STARCH HYDROLYSATE, BUTYLENE GLYCOL, GLYCERIN, LEONURUS SIBIRICUS EXTRACT, ORYZA SATIVA (RICE) BRAN EXTRACT, DENDROBIUM CANDIDUM EXTRACT, CYNANCHUM ATRATUM EXTRACT, ASCORBIC ACID, CARBOMER, TRIETHANOLAMINE, SODIUM HYALURONATE, HYDROXYACETOPHENONE, 1,2-HEXANEDIOL